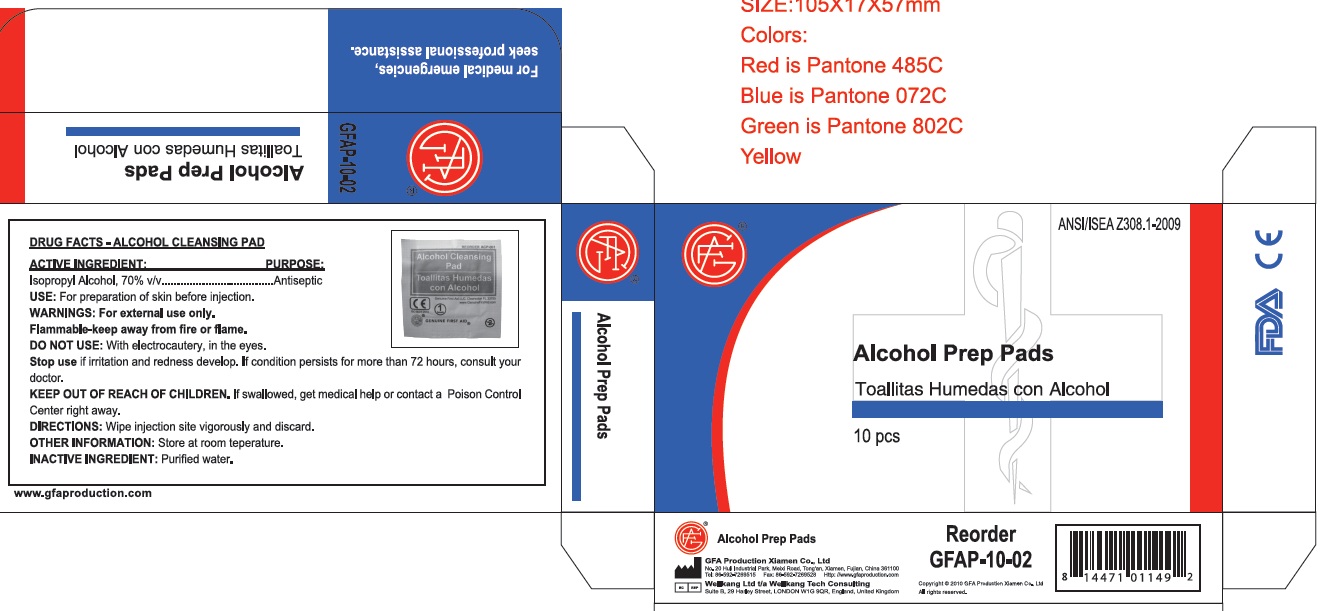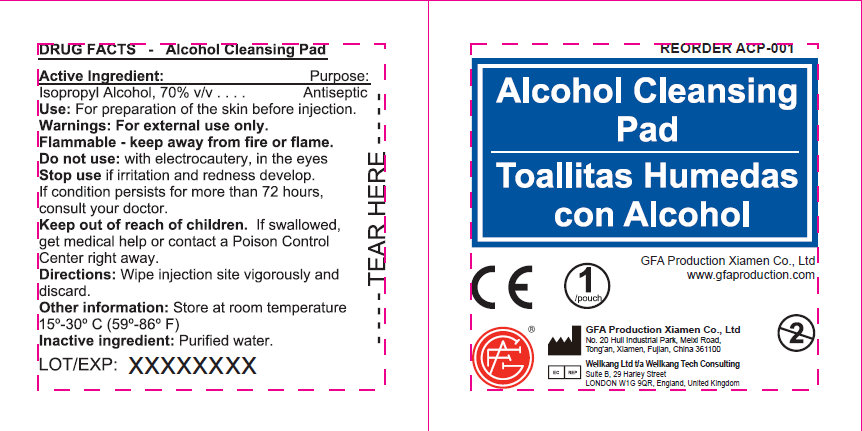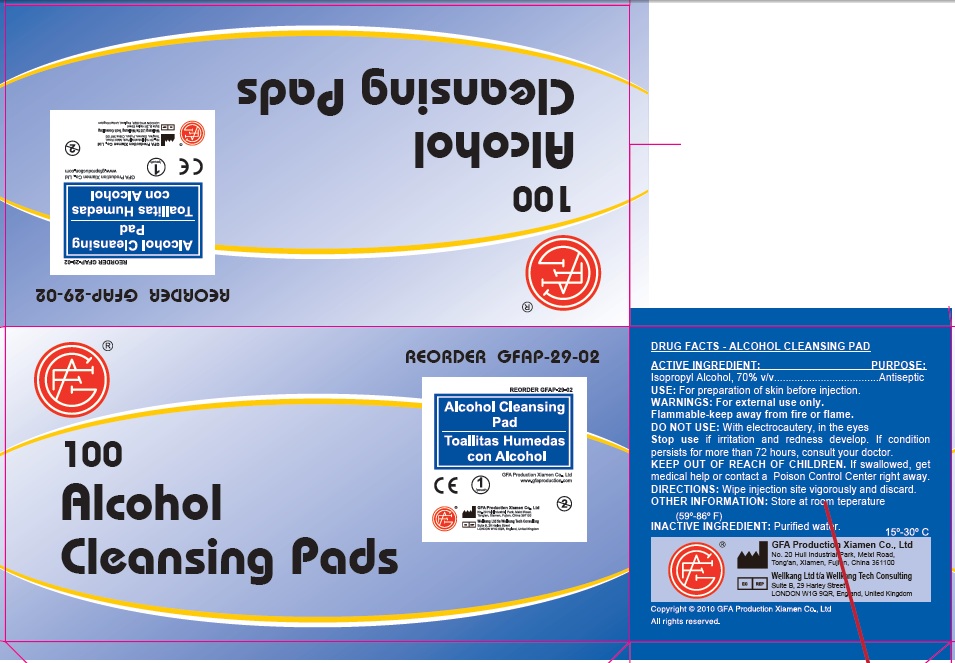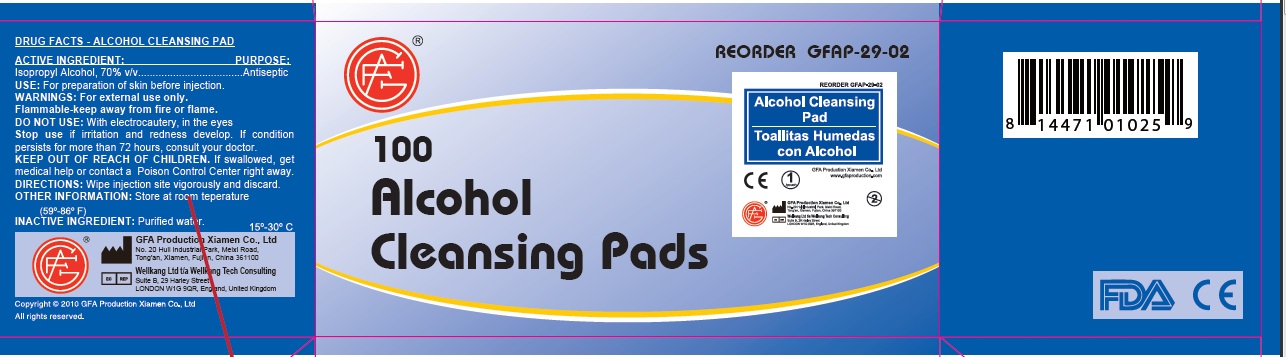 DRUG LABEL: Alcohol Cleansing Pad
NDC: 52124-0002 | Form: LIQUID
Manufacturer: Genuine First Aid LLC
Category: otc | Type: HUMAN OTC DRUG LABEL
Date: 20191205

ACTIVE INGREDIENTS: ISOPROPYL ALCOHOL 70 mL/100 mL
INACTIVE INGREDIENTS: WATER

Alcohol Cleansing Pad

Active Ingredient

Isopropyl Alcohol, 70% v/v

Purpose

Antiseptic

Use

For preparation of skin before injection.

Warnings

For external use only.

STORAGE AND HANDLING

Flammable - keep away from fire or flame

Store at room temperature 15-30 degree Celsius (59-86 degree Fahrenheit)

Do not use: with electrocautery, in the eyes.

Stop use if irritation and redness develop. If condition persists for more than 72 hours, consult your doctor.

Keep out of reach of children. If swallowed,

get medical help or contact a Poison Control

Center right away.

Directions

Wipe Injection site vigorously and discard.

Inactive Ingredient

Purified water.

LOT/EXP: Made in CHINA

20140301

PACKAGE LABEL

Alcohol Cleansing Pad

Genuine First Aid LLC, Clearwater FL 33755

www.GenuineFirstAid.com

1/pouch

GENUINE FIRST AID

100 Alcohol cleansing pads

Reorder GFAP-39-02